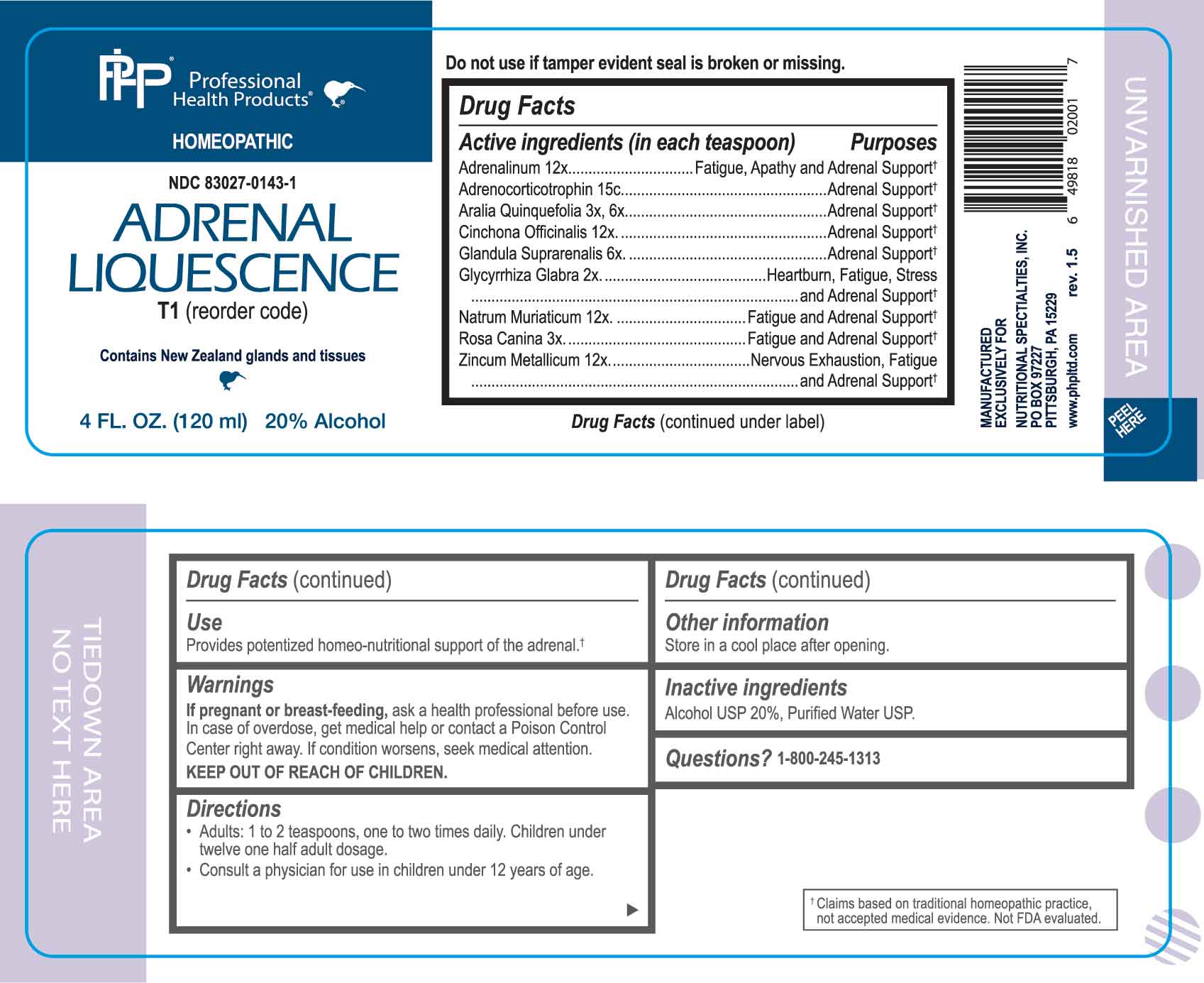 DRUG LABEL: Adrenal Liquescence
NDC: 83027-0143 | Form: LIQUID
Manufacturer: Nutritional Specialties, Inc.
Category: homeopathic | Type: HUMAN OTC DRUG LABEL
Date: 20250226

ACTIVE INGREDIENTS: GLYCYRRHIZA GLABRA 2 [hp_X]/1 mL; ROSA CANINA FRUIT 3 [hp_X]/1 mL; AMERICAN GINSENG 3 [hp_X]/1 mL; BOS TAURUS ADRENAL GLAND 6 [hp_X]/1 mL; EPINEPHRINE 12 [hp_X]/1 mL; CINCHONA OFFICINALIS BARK 12 [hp_X]/1 mL; SODIUM CHLORIDE 12 [hp_X]/1 mL; ZINC 12 [hp_X]/1 mL; CORTICOTROPIN 15 [hp_C]/1 mL
INACTIVE INGREDIENTS: WATER; ALCOHOL

DRUG FACTS:

ACTIVE INGREDIENTS:

(in each teaspoon) Adrenalinum 12X, Adrenocorticotrophin 15C, Aralia Quinquefolia 3X, 6X, Cinchona Officinalis 12X, Glandula Suprarenalis 6X, Glycyrrhiza Glabra 2X, Natrum Muriaticum 12X, Rosa Canina 3X, Zincum Metallicum 12X.

PURPOSE:

Adrenalinum – Fatigue, Apathy and Adrenal Support,† Adrenocorticotrophin – Adrenal Support,† Aralia Quinquefolia - Adrenal Support,† Cinchona Officinalis - Adrenal Support,† Glandula Suprarenalis - Adrenal Support,† Glycyrrhiza Glabra – Heartburn, Fatigue, Stress and Adrenal Support,† Natrum Muriaticum – Fatigue and Adrenal Support,† Rosa Canina – Fatigue and Adrenal Support,† Zincum Metallicum – Nervous Exhaustion, Fatigue and Adrenal Support†

USES:

Provides potentized homeo-nutritional support of the adrenal.†

†Claims based on traditional homeopathic practice, not accepted medical evidence. Not FDA evaluated.

WARNINGS:

If pregnant or breast-feeding, ask a health professional before use.

In case of overdose, get medical help or contact a Poison Control Center right away.

If condition worsens, seek medical attention.

KEEP OUT OF REACH OF CHILDREN

Do not use if tamper evident seal is broken or missing.

Store in a cool place after opening

KEEP OUT OF REACH OF CHILDREN:

In case of overdose, get medical help or contact a Poison Control Center right away.

DIRECTIONS:

• Adults: 1 to 2 teaspoons, one to two times daily. Children under twelve one half adult dosage.

• Consult a physician for use in children under 12 years of age.

INACTIVE INGREDIENTS:

Alcohol USP 20%, Purified Water USP.

QUESTIONS:

MANUFACTURED EXCLUSIVELY FOR

NUTRITIONAL SPECIALTIES, INC.

PO BOX 97227

PITTSBURG, PA 15229

www.phpltd.com

PACKAGE LABEL DISPLAY:

Professional

Health Products

HOMEOPATHIC

NDC 83027-0143-1

ADRENAL LIQUESCENCE

4 FL. OZ (120 ml)